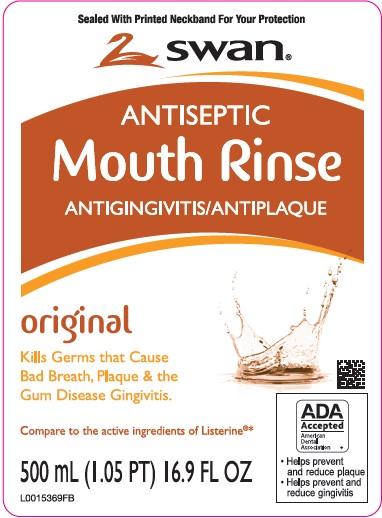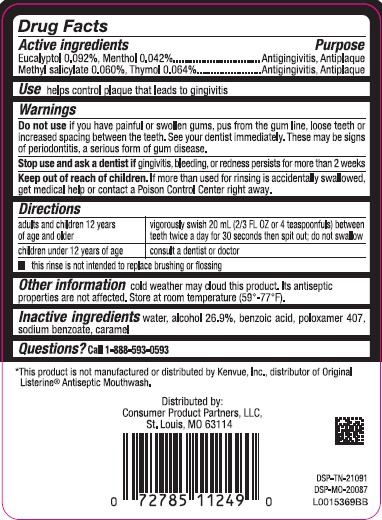 DRUG LABEL: Antiseptic Mouth Rinse
NDC: 11344-318 | Form: MOUTHWASH
Manufacturer: Consumer Product Partners, LLC
Category: otc | Type: HUMAN OTC DRUG LABEL
Date: 20250421

ACTIVE INGREDIENTS: EUCALYPTOL 0.92 mg/1 mL; MENTHOL 0.42 mg/1 mL; METHYL SALICYLATE 0.6 mg/1 mL; THYMOL 0.64 mg/1 mL
INACTIVE INGREDIENTS: SODIUM BENZOATE; CARAMEL; POLOXAMER 407; WATER; ALCOHOL; BENZOIC ACID

Swan 318.003/318AH-AI
Antiseptic Mouthrinse

Active ingredients

Eucalyptol 0.092%

Menthol 0.042%

Methyl salicylate 0.060%

Thymol 0.064%

Purpose

Antiginvitis, Antiplaque

Use

helps control plaque that leads to gingivitis

Warnings

For this product

Do not use

if you have painful or swollen gums, pus from the gum line, loose teeth or increased spacing between the teeth. See your dentist immediately. These may be signs of periodontitis, a serious form of gum disease.

Stop use and ask a dentist if

gingivitis, bleeding, or redness persists for more than 2 weeks

Keep out of reach of children.

If more than used for rinsing is accidentally swallowed, get medical help or contact a Poison Control Center right away.

Directions

adults and children 12 years of age and older - vigorously swish 20 mL between teeth twice a day for 30 seconds then spit out; do not swallow
children under 12 years of age - consult a dentist or doctor

- this rinse is not intended to replace brushing or flossing

Other information

cold weather may cloud this product. Its antiseptic properties are not affected. Store at room temperature (59°-77°F).

Inactive ingredients

water, alcohol 26.9%, benzoic acid, poloxamer 407, sodium benzoate, caramel

QUESTIONS?

Call 1-888-593-0593

Disclaimer

*This product is not manufactured or distributed by Kenvue, Inc, distributor of Original Listerine® Antiseptic Mouthwash.

Adverse reaction

Distributed by:

Consumer Product Partners, LLC,

St. Louis, MO 63114

DSP-TN-21091

DSP-MO-20087

Principal panel display

SEALED WITH PRINTED NECKBAND FOR YOUR PROTECTION

swan®

ANTISEPTIC

Mouth Rinse

ANTIGINGIVITIS/ANTIPLAQUE

original

Kills Germs that Cause Bad Breath, Plaque & the Gum & The Gum Disease Gingivitis.

Compare to the active ingredients of Listerine®*

ADA Accepted

American Dental Association

- Helps prevent and reduce reduce plaque
- Helps prevent and reduce gingivitis

500 mL (1.05 PT) 16.9 FL OZ